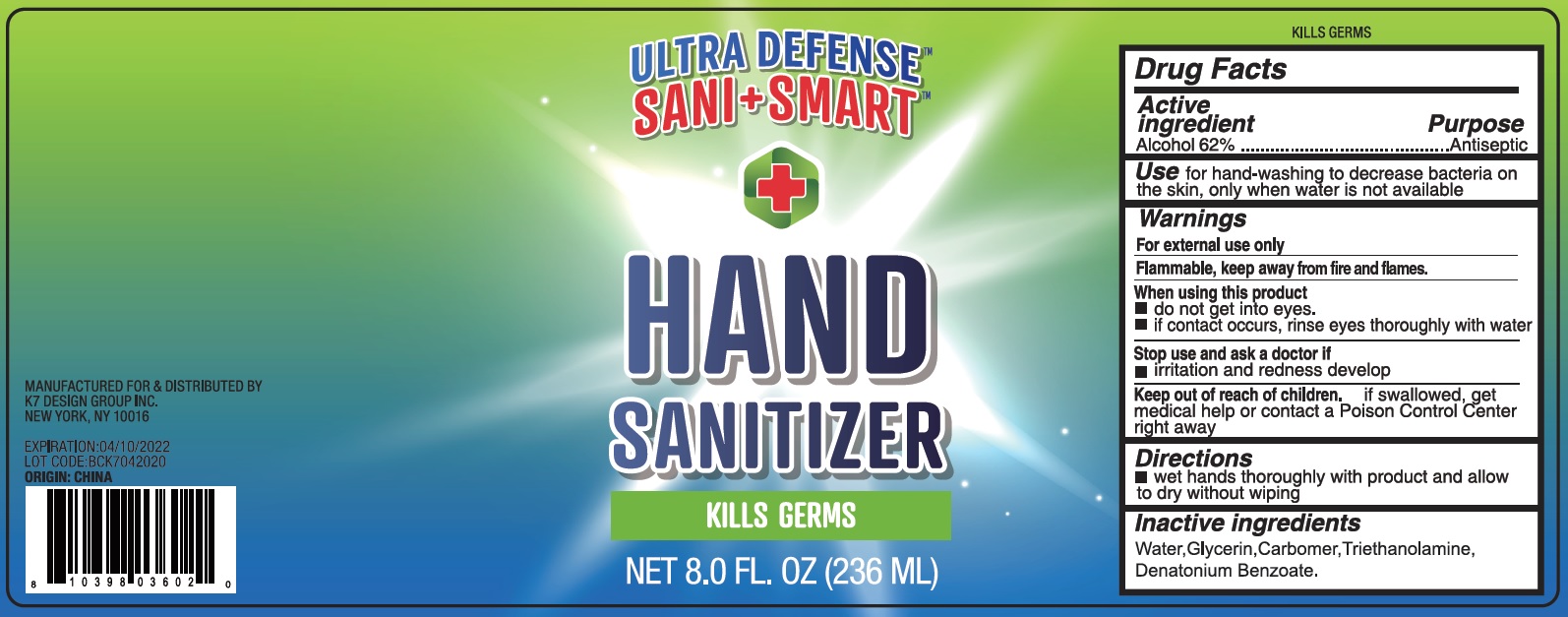 DRUG LABEL: Hand Sanitizer
NDC: 74177-021 | Form: GEL
Manufacturer: K7 Design Group Inc.
Category: otc | Type: HUMAN OTC DRUG LABEL
Date: 20231026

ACTIVE INGREDIENTS: ALCOHOL 0.62 mL/1 mL
INACTIVE INGREDIENTS: WATER; GLYCERIN; CARBOMER HOMOPOLYMER, UNSPECIFIED TYPE; TROLAMINE; DENATONIUM BENZOATE

Hand Sanitizer

Active ingredient

Alcohol 62%

Purpose

Antiseptic

Use

for hanw-ashing to decrease bacteria on the skin, only when water is not available

Warnings

For external use only Flammable, keep away from fire and flames.

When using this product

- do not get into eyes.
- if contact occurs, rinse eyes thoroughly with water

Stop use and ask a doctor if

- irritation and redness develop

Keep out of reach of children.

if swallowed, get medical help or contact a Poison Contorl Center right away

Directions

- Wet hands thoroughly with product and allow to dry without wiping

Inactive ingredients

Water,Glycerin, Carbomer, Triethanolamine, Denatonium Benzoate.